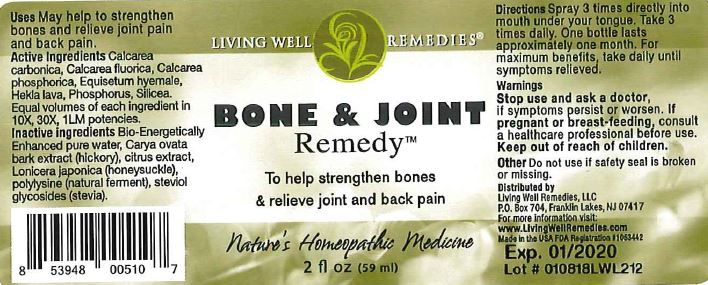 DRUG LABEL: Bone and Joint Remedy
NDC: 53852-0012 | Form: LIQUID
Manufacturer: Living Well Remedies, LLC
Category: homeopathic | Type: HUMAN OTC DRUG LABEL
Date: 20180216

ACTIVE INGREDIENTS: OYSTER SHELL CALCIUM CARBONATE, CRUDE 10 [hp_X]/59 mL; CALCIUM FLUORIDE 10 [hp_X]/59 mL; TRIBASIC CALCIUM PHOSPHATE 10 [hp_X]/59 mL; EQUISETUM HYEMALE 10 [hp_X]/59 mL; HEKLA LAVA 10 [hp_X]/59 mL; PHOSPHORUS 10 [hp_X]/59 mL; SILICON DIOXIDE 10 [hp_X]/59 mL
INACTIVE INGREDIENTS: WATER; CARYA OVATA BARK; CITRUS BIOFLAVONOIDS; LONICERA JAPONICA FLOWER; POLYEPSILON-LYSINE (4000 MW); REBAUDIOSIDE A

Bone and Joint Remedy

DOSAGE AND ADMINISTRATION

Directions: Spray 3 times directly into mouth under your tongue. Take 3 times daily. One bottle lasts approximately one month. For maximum benefits, take daily until symptoms relieved.

WARNINGS

Warnings: Stop use and ask a doctor, if symptoms persist or worsen. If pregnant or breast-feeding, consult a healthcare professional before use.

Keep out of reach of children.

OTHER SAFETY INFORMATION

Other: Do not use if safety seal is broken or missing.

PURPOSE

Uses: May help to strengthen bones and relieve joint pain and back pain.

ACTIVE INGREDIENT

Ingredients: Calcarea carbonica, Calcarea fluorica, Calcarea phosphorica, Equisetum hyemale, Hekla lava, Phosphorus, Silicea.

Equal volumes of each ingredient in 10X, 30X, 1LM potencies.

INACTIVE INGREDIENT

Inactive ingredients: Bio-Energetically enhanced pure water, Carya ovata bark extract (hickory), citrus extract, Lonicera japonica (honeysuckle), polylysine (natural ferment), steviol glycoside (stevia)

INDICATIONS AND USAGE

Uses: May help to:

- strengthen bones
- relieve joint pain
- back pain